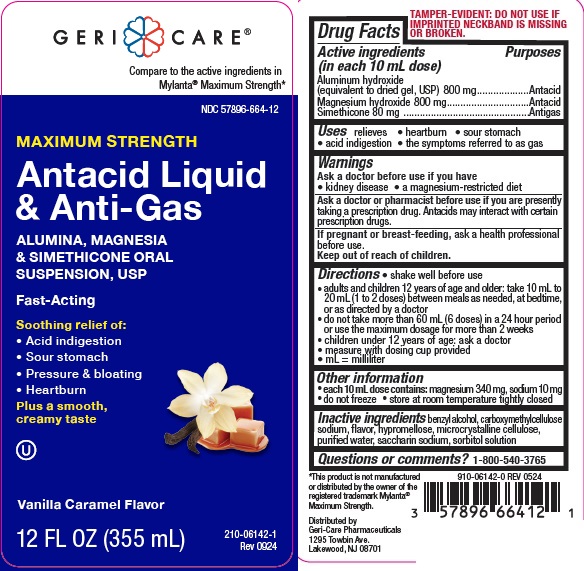 DRUG LABEL: MAXIMUM STRENGTH Antacid
NDC: 57896-664 | Form: SUSPENSION
Manufacturer: Geri-Care Pharmaceuticals, Corp
Category: otc | Type: HUMAN OTC DRUG LABEL
Date: 20241209

ACTIVE INGREDIENTS: ALUMINUM HYDROXIDE 400 mg/5 mL; MAGNESIUM HYDROXIDE 400 mg/5 mL; DIMETHICONE 40 mg/5 mL
INACTIVE INGREDIENTS: BENZYL ALCOHOL; CARBOXYMETHYLCELLULOSE SODIUM; HYPROMELLOSES; CELLULOSE, MICROCRYSTALLINE; WATER; SACCHARIN SODIUM; SORBITOL SOLUTION

gc 664 mylanta vanilla

Active ingredients (in each 10 mL dose)

Aluminum hydroxide 800 mg (equivalent to dried gel, USP)
Magnesium hydroxide 800 mg
Simethicone 80 mg

Purposes

Antacid

Antigas

Uses

relieves

- heartburn
- sour stomach
- acid indigestion
- the symptoms referred to as gas

Warnings

Ask a doctor before use if you have

- kidney disease
- a magnesium-restricted diet

Ask a doctor or pharmacist before use if you are

taking a prescription drug.
Antacids may interact with certain prescription drugs.

If pregnant or breast-feeding,

ask a health professional before use.

Keep out of reach of children.

Directions

- shake well before use
- adults and children 12 years of age and older: take 10 mL to 20 mL (1 to 2 doses) between meals as needed, at bedtime,

or as directed by a doctor

- do not take more than 60 mL (6 doses) in a 24 hour period or use the maximum dosage for more than 2 weeks
- children under 12 years of age: ask a doctor
- measure with dosing cup provided
- mL = milliliter

Other information

- each 10 mL dose contains: magnesium 340 mg, sodium 10 mg
- do not freeze
- store at room temperature tightly closed

Inactive ingredients

benzyl alcohol, carboxymethylcellulose sodium, flavor, hypromellose, microcrystalline cellulose,
purified water, saccharin sodium, sorbitol solution

Questions or comments?

1-800-540-3765